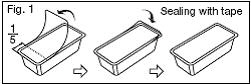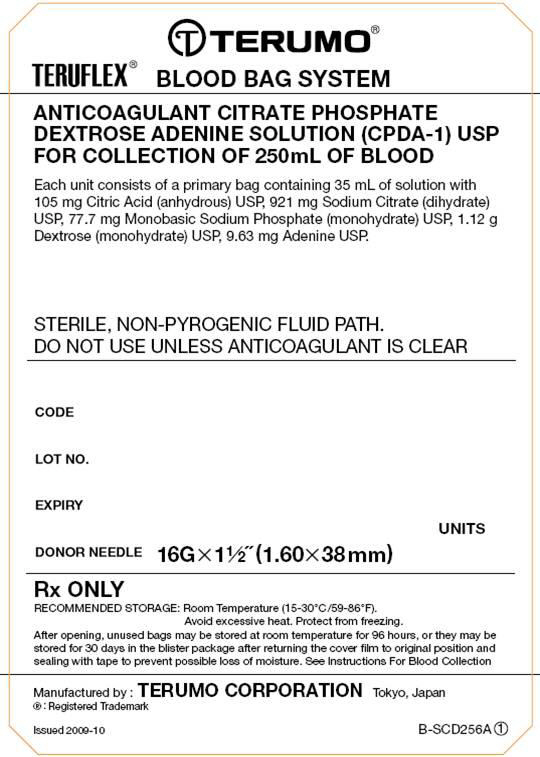 DRUG LABEL: TERUFLEX Blood Bag System Anticoagulant Citrate Phosphate Dextrose Adenine (CPDA-1)
NDC: 53877-001 | Form: SOLUTION
Manufacturer: Terumo Corporation
Category: prescription | Type: HUMAN PRESCRIPTION DRUG LABEL
Date: 20181206

ACTIVE INGREDIENTS: Anhydrous Citric Acid 2.99 g/1000 mL; Trisodium Citrate Dihydrate 26.3 g/1000 mL; SODIUM PHOSPHATE, MONOBASIC, MONOHYDRATE 2.22 g/1000 mL; Dextrose Monohydrate 31.9 g/1000 mL; Adenine 0.275 g/1000 mL
INACTIVE INGREDIENTS: Water

TERUFLEX® BLOOD BAG SYSTEM
CPDA-1 SOLUTION

INDICATIONS AND USAGE

For the collection of 250 mL of Whole Blood

Revised 2015-12 N-BB-A 3

FULL PRESCRIBING INFORMATION
*Sections or subsections omitted from the Full Prescribing Information are not listed [includes sections 4, 6, 7, 8, 9, 10, 12, 13, 14, 15 and 17].
1. INDICATIONS AND USAGE
1.1. Read these instructions carefully before use.
1.2. Rx ONLY.
1.3. Intended for the collection, processing and preservation of Whole Blood and blood components. Not intended for direct intravenous infusion.
1.4. For the collection of 250 mL ±10% Whole Blood:
1.4.1. From elderly, pediatric, or smaller autologous donors who may not tolerate larger blood collections.
1.4.2. For blood collections as directed by a patient's physician.
1.5. NOTE: Production of Platelets and Plasma is not intended with this product.

2. DOSAGE AND ADMINISTRATION

2.1. To open blister package, peel cover film back 4/5 of its length.

2.2. Prepare the blood bag following your institution's standard operating procedures.

2.3. Make a loose knot in the donor tubing approximately 10 cm or 4 inches from the needle unless alternate methods are used to seal the tubing at the end of collection.

2.4. Temporarily clamp donor tubing.

2.5. Suspend the collection bag as far as possible below the donor's arm.

2.6. Apply blood pressure cuff or tourniquet to donor's arm. Disinfect site of phlebotomy according to institutional standard operating procedures. If blood pressure cuff is used, inflate to approximately 60 mmHg.

2.7. Remove the needle cover and perform phlebotomy.

2.7.1. CAUTION: Do not touch the needle after removing the needle cover.

2.8. Remove the temporary clamp on the donor tubing to permit blood flow into the collection bag.

2.9. Secure donor tubing to donor's arm.

2.10. Mix blood with anticoagulant in the collection bag and continue to mix at several intervals during collection and immediately after collection. If using an automated mixer, follow manufacturer's instructions.

2.11. Collect labeled volume of blood 250 mL ±10%.

2.12. When the desired amount of blood has been collected, seal the tubing or tighten the loose knot (white knot) prepared in Step 2.3. Temporarily clamp between the knot and needle. Sever donor tubing between knot and clamp. Alternate methods may be used to seal tubing. Collect blood samples using careful attention to aseptic technique and following your institution's standard operating procedures.

2.12.1. CAUTION: Do not use a dielectric tube sealer to seal the tubing while the needle is connected to the donor's body unless it is approved for such a purpose.

2.13. Reapply clamp to donor tubing; release pressure on donor's arm and remove needle. If using a needle safety device, follow manufacturer's instructions.

2.13.1. CAUTION: Discard phlebotomy needle/donor tubing according to institutional standard operating procedures.

2.14. Immediately after collection, invert collection bag several times to assure blood and anticoagulant are well mixed.

2.15. Strip blood from donor tubing into collection bag, mix well, and allow tubing to refill; repeat once. To prevent the blood from clotting in the tubing, work quickly as possible. Make an appropriate number of segments of anticoagulated blood for testing by sealing on or near the X marks. Leave segments attached to Whole Blood unit.

2.16. Store CPDA-1 Whole Blood (or Red Blood Cells) between 1 – 6 ° C for up to 35 days.

2.17. For further preparation and processing of other components, use standard processing and storage techniques following approved regulations and standards.

2.17.1. NOTE: Production of Platelets and Plasma is not intended with this product.

3. DOSAGE FORMS AND STRENGTHS

3.1. 35 mL Citrate Phosphate Dextrose Adenine (CPDA-1) anticoagulant USP for collection of 250 mL Whole Blood. Each 35 mL contains 105mg Citric Acid (anhydrous) USP, 921mg Sodium Citrate (dihydrate) USP, 77.7mg Monobasic Sodium Phosphate (monohydrate) USP, 1.12g Dextrose (monohydrate) USP and 9.63mg Adenine USP.

5. WARNINGS AND PRECAUTIONS

5.1. Rx ONLY.

5.2. Do not use unless solutions are clear and free from particulates.

5.3. Always inspect the blood bag set for leaks before use.

5.4. Avoid excessive heat and direct sunlight. Protect from freezing.

5.5. Recommended storage conditions: Room Temperature (15-30°C/59-86°F).

5.6. It is normal to have condensation in the blister packaging. If the amount of moisture is greater than expected, check for leaks from the fluid-filled components of the blood bag set.

5.7. Use aseptic techniques.

5.8. Do not use a dielectric tube sealer to seal the tubing while the needle is connected to the donor's body unless it is approved for such a purpose.

5.9. Do not touch needle after removing the needle cover.

5.10. Discard phlebotomy needle/donor tubing according to institutional standard operating procedures.

5.11. The AGELESS® (oxygen absorber packet, Mitsubishi Gas Chemical) contained in this package absorbs oxygen and generates heat on removal. Do not open and handle it with care.

5.12. Dispose of the AGELESS packet with the blister tray.

5.13. Do not dispose the AGELESS packet with wastes containing volatile or flammable materials.

5.14. Due to possible exposure to infectious agents in the handling of blood, take adequate precautions at all times to prevent exposure to and transmission of such agents. Follow your institution's standard operating procedures.

11. DESCRIPTION

11.1. This blood bag system includes a 16 gauge x 1 1/2 inch (1.60 x 38 mm) needle with needle cover and a 250 mL (nominal capacity 300 mL) collection bag containing 35 mL Citrate Phosphate Dextrose Adenine (CPDA-1) anticoagulant.

11.2. The blood bag collection set is made of PVC (polyvinyl chloride with DEHP plasticizer).

11.3. The blood bag has no components made of natural rubber latex.

11.4. Tubing internal diameter (ID) nominal 3.0 mm.

11.5. Tubing outer diameter (OD) nominal 4.4 mm.

11.6. Donor tubing line maximum 12 segments available.

16. HOW SUPPLIED/STORAGE AND HANDLING

16.1. Single use only.

16.2. Sterile and non-pyrogenic fluid path. Sterilized by steam. Opacity of the blood bag system may be observed. This is due to moisture absorption during the sterilization process. This is normal and does not affect the solution quality or safety. The opacity will diminish gradually.

16.3. A Material Safety Data Sheet (MSDS) is not required for this product.

16.4. Recommended storage conditions: Room Temperature (15-30°C/59-86°F).

16.5. Avoid excessive heat and direct sunlight. Protect from freezing.

16.6. To open blister package, peel cover film back 4/5 of its length.

16.7. After opening the blister package, unused blood bags may be stored at room temperature for 96 hours or they may be stored for 30 days by returning cover film to original position and sealing with tape to prevent evaporation of solutions.

16.8. Blood bags in the unopened blister package may be used through the last day of the month and year as indicated on the original manufacturer's packaging.

16.9. The AGELESS packet contained in this package absorbs oxygen and generates heat on removal. Do not open and handle it with care.

16.10. Dispose of the AGELESS packet with the blister tray.

16.11. Do not dispose the AGELESS packet with wastes containing volatile or flammable materials.

16.12. The Single blood bag set, Code BB＊SCD256A, is supplied 90/case.

MANUFACTURED BY: TERUMO CORPORATION
44-1, 2-CHOME, HATAGAYA, SHIBUYA-KU, TOKYO 151-0072, JAPAN MADE IN JAPAN
（R）: Registered Trademark
©TERUMO CORPORATION December, 2015

AGELESS is a registered trademark of MITSUBISHI GAS CHEMICAL CO., INC.

Tray/Case Label
TERUFLEX® BLOOD BAG SYSTEM
ANTICOAGULANT CITRATE PHOSPHATE
DEXTROSE ADENINE SOLUTION (CPDA-1) USP
FOR COLLECTION OF 250mL OF BLOOD
Each unit consists of a primary bag containing 35 mL of solution with
105 mg Citric Acid (anhydrous) USP, 921 mg Sodium Citrate (dihydrate)
USP, 77.7 mg Monobasic Sodium Phosphate (monohydrate) USP, 1.12 g
Dextrose (monohydrate) USP, 9.63 mg Adenine USP.
STERILE, NON-PYROGENIC FLUID PATH.
DO NOT USE UNLESS ANTICOAGULANT IS CLEAR
CODE
LOT No.
EXPIRY
UNIT(S)
DONOR NEEDLE 16G X 1 1/2˝ (1.60 X 38mm)
Rx ONLY
RECOMMENDED STORAGE: Room Temperature (15-30°C/59-86°F).
Avoid excessive heat. Protect from freezing.
After opening, unused bags may be stored at room temperature for 96 hours, or they may be
stored for 30 days in the blister package after returning the cover film to original position and
sealing with tape to prevent possible loss of moisture. See Instructions For Blood Collection
Manufactured by : TERUMO CORPORATION Tokyo, Japan
® : Registered Trademark
Issued 2009 -10

Image of Label: